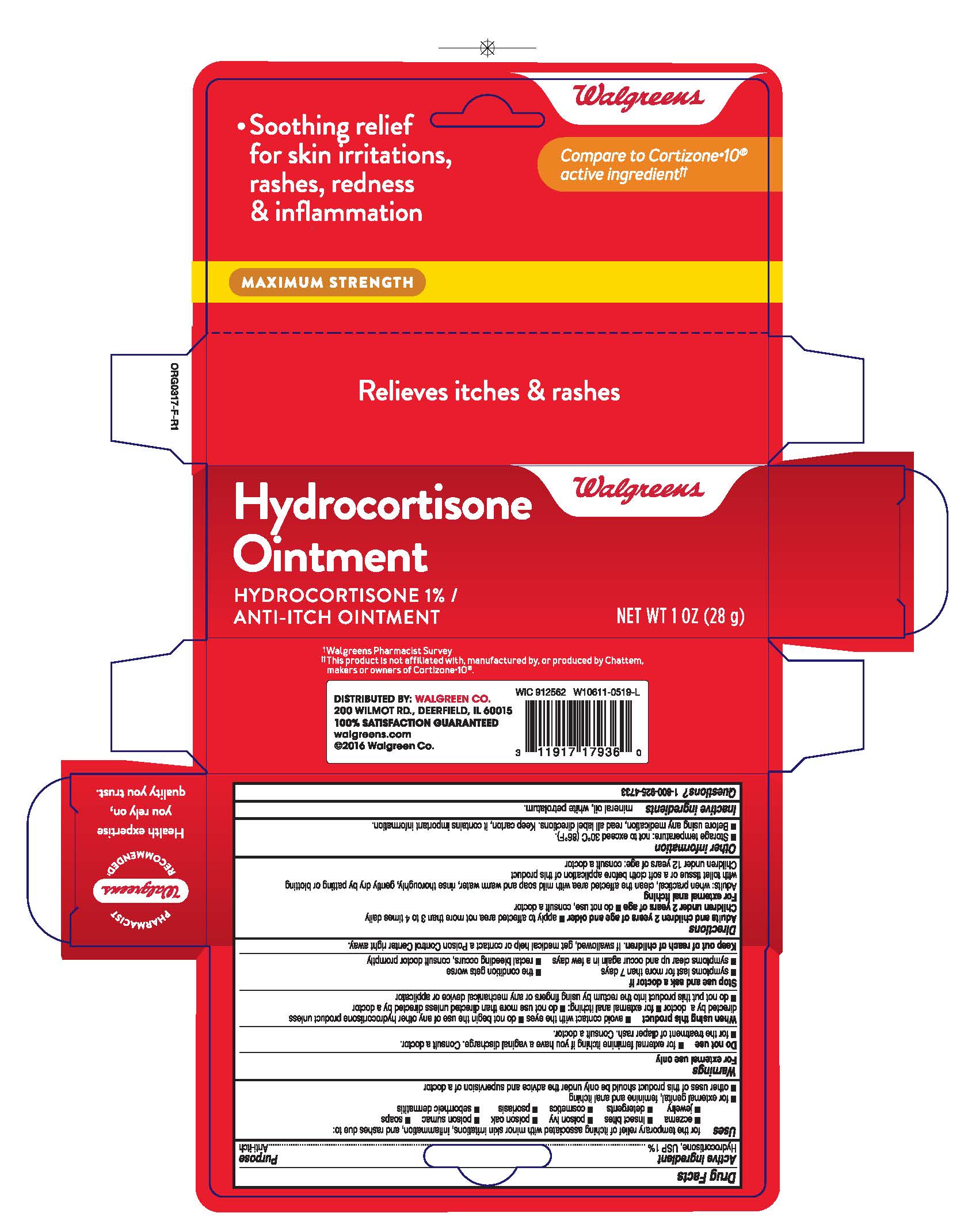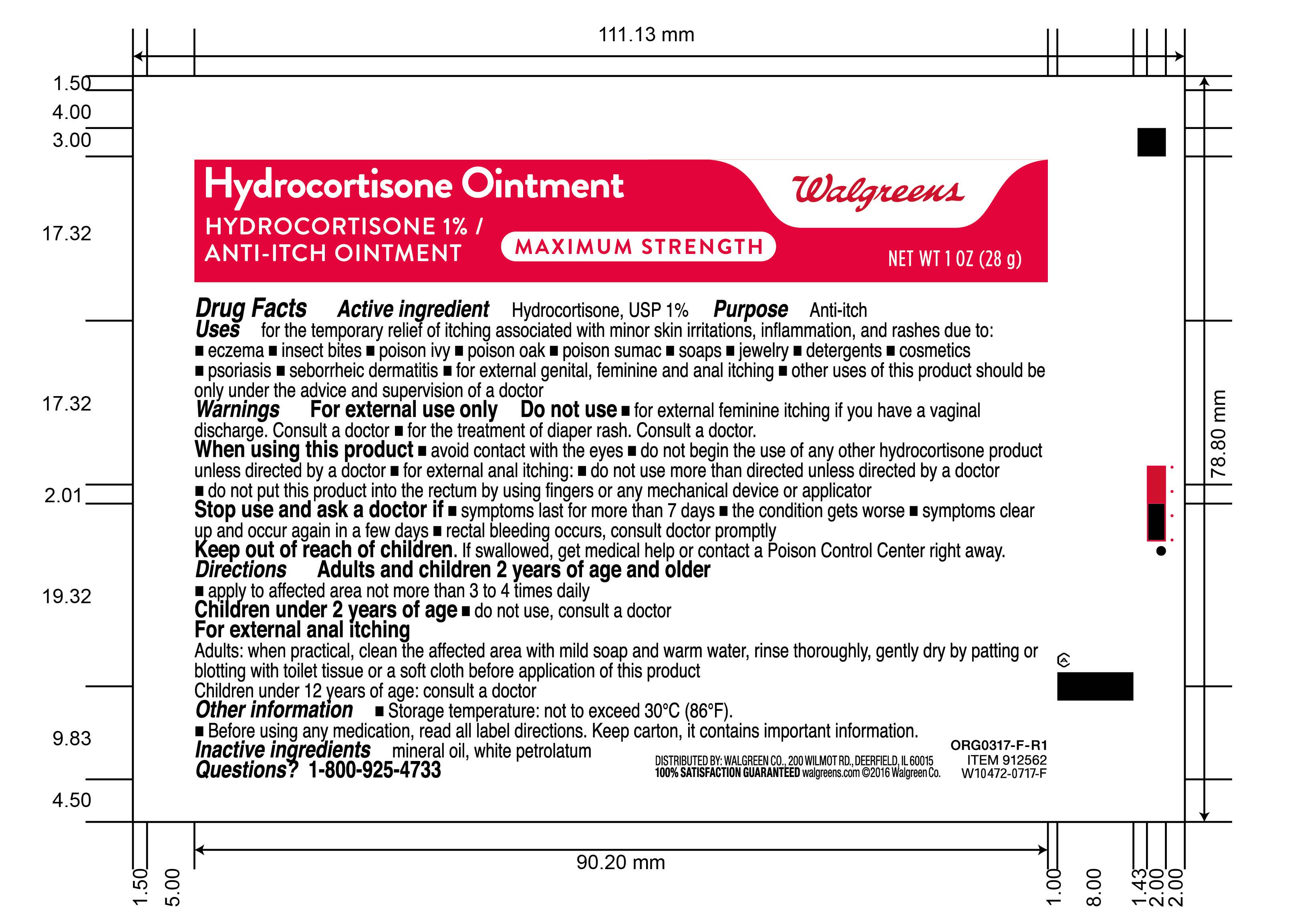 DRUG LABEL: Maximum Strength Hydrocortisone
NDC: 0363-0230 | Form: OINTMENT
Manufacturer: Walgreens
Category: otc | Type: HUMAN OTC DRUG LABEL
Date: 20260115

ACTIVE INGREDIENTS: HYDROCORTISONE 1 g/100 g
INACTIVE INGREDIENTS: PETROLATUM; MINERAL OIL

Walgreens® 1% Hydrocortisone Ointment 1oz

Active Ingredient

Hydrocortisone, USP 1%

Purpose

Anti-itch

Uses

for the temporary relief of itching associated with minor skin irritations, inflammation, and rashes due to: eczema, insect bites, poison ivy, poison oak, poison sumac, soaps, jewelry, detergents, cosmetics, psoriasis, seborrheic dermatitis, for external genital, feminine and anal itching, other uses of this product should be only under the advice and supervision of a doctor

Warnings

For external use only

Do not use

for external feminine itching if you have a vaginal discharge. Consult a doctor.

for the treatment of diaper rash. Consult a doctor.

When using this product

avoid contact with the eyes, do not begin the use of any other hydrocortisone product unless directed by a doctor, for external anal itching: do not use more than directed unless directed by a doctor, do not put this product into the rectum by using fingers or any mechanical device or applicator

Stop use and ask a doctor if

symptoms last for more than 7 days, the condition gets worse, symptoms clear up and occur again in a few days, rectal bleeding occurs, consult doctor promptly

Keep out of reach of children.

If swallowed, get medical help or contact a Poison Control Center right away.

Directions

Adults and children 2 years of age and older * apply to affected area not more than 3 to 4 times daily.

Children under 2 years of age * do not use, consult a doctor.

For external anal itching - Adults: when practical, clean the affected area with mild soap and warm water, rinse thoroughly, gently dry by patting or blotting with toilet tissue or a soft cloth before applicaion of this product.

Children under 12 years of age: consult a doctor.

Other information

Storage temperature: not to exceed 30oC (86oF).

Before using any medication, read all label directions. Keep carton, it contains important information.

Inactive Ingredients

mineral oil, white petrolatum